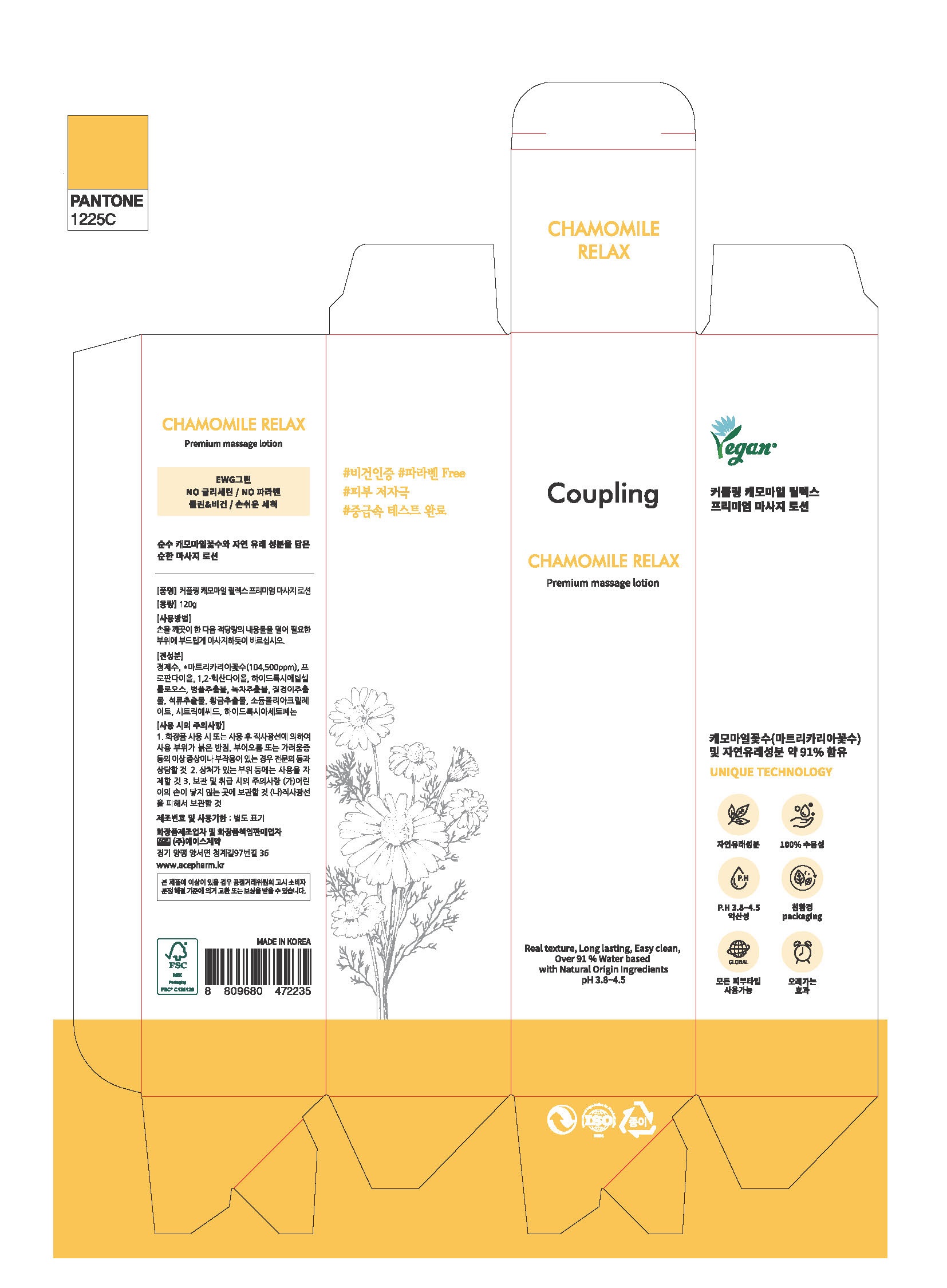 DRUG LABEL: Coupling Chamomile Relax Premium massagelotion
NDC: 74196-0005 | Form: LOTION
Manufacturer: ACE PHARMACEUTICAL CO LTD
Category: otc | Type: HUMAN OTC DRUG LABEL
Date: 20220113

ACTIVE INGREDIENTS: PROPANEDIOL 2 g/100 g
INACTIVE INGREDIENTS: WATER

Drug Facts

ACTIVE INGREDIENT

PROPANEDIOL

INACTIVE INGREDIENT

green tea extract, citric acid, etc.

PURPOSE

skin protectant

KEEP OUT OF REACH OF THE CHILDREN

INDICATIONS AND USAGE

apply proper amount to the skin and gently massage

WARNINGS

For external use only.

When using this product keep out of eyes. If contact with eyes occurs, rinse promptly and thoroughly with water.

Stop use and ask a doctor if significant irritation or sensitization develops.

Keep out of reach of children. If swallowed, get medical help or contact a Poison Control Center right away.

DOSAGE AND ADMINISTRATION

for external use only